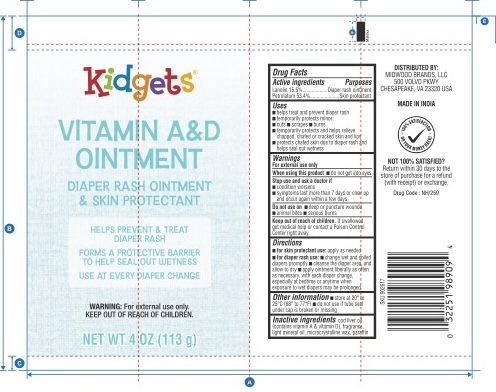 DRUG LABEL: Kidgets Baby Petroleum Jelly
NDC: 51628-4248 | Form: OINTMENT
Manufacturer: MY IMPORTS USA LLC
Category: otc | Type: HUMAN OTC DRUG LABEL
Date: 20250822

ACTIVE INGREDIENTS: PETROLATUM 53.4 g/100 g; LANOLIN 15.5 g/100 g
INACTIVE INGREDIENTS: PARAFFIN; MICROCRYSTALLINE WAX; COD LIVER OIL; LIGHT MINERAL OIL

Kidgets Vitamin A & D

Active Ingredient

Lanolin 15.5%

Petrolatum 53.4%

Purpose

Diaper rash ointment

Skin protectant

Uses

■ helps treat and prevent diaper rash ■ temporarily protects minor cuts, scrapes and burns ■ temporarily protects and relieve chapped,chafed or cracked skin or lips■ protects chafed skin due to diaper rash and helps seal out wetness

Warnings

For external use only

When using this product

■ do not get into eyes

Stop use and ask a doctor if

■ condition worsens ■ symptoms last more than 7 days or clear up and occur again within a few days

Do not use on

■ deep or puncture wounds ■ animal bites ■ serious burns

Keep out of reach of children

If swallowed, get medical help or contact a Poison Control Center right away

Directions

■ for skin protectant use: ■ apply as needed ■ for diaper rash: ■ change wet and soiled diapers promptly ■ cleanse the diaper area and allow to dry ■ apply ointment liberally as often as necessary, with each diaper change, especially at bedtime or anytime when exposure to wet diapers may be prolonged

Other information

■ store at 20 to 25C (68-77F) ■ do not use if tube seal under cap is broken, missing or if tube tip is cut prior to opening

Inactive ingredients

cod liver oil (contains vitamin A and vitamin D), fragrance, light mineral oil, microcrystalline wax, paraffin